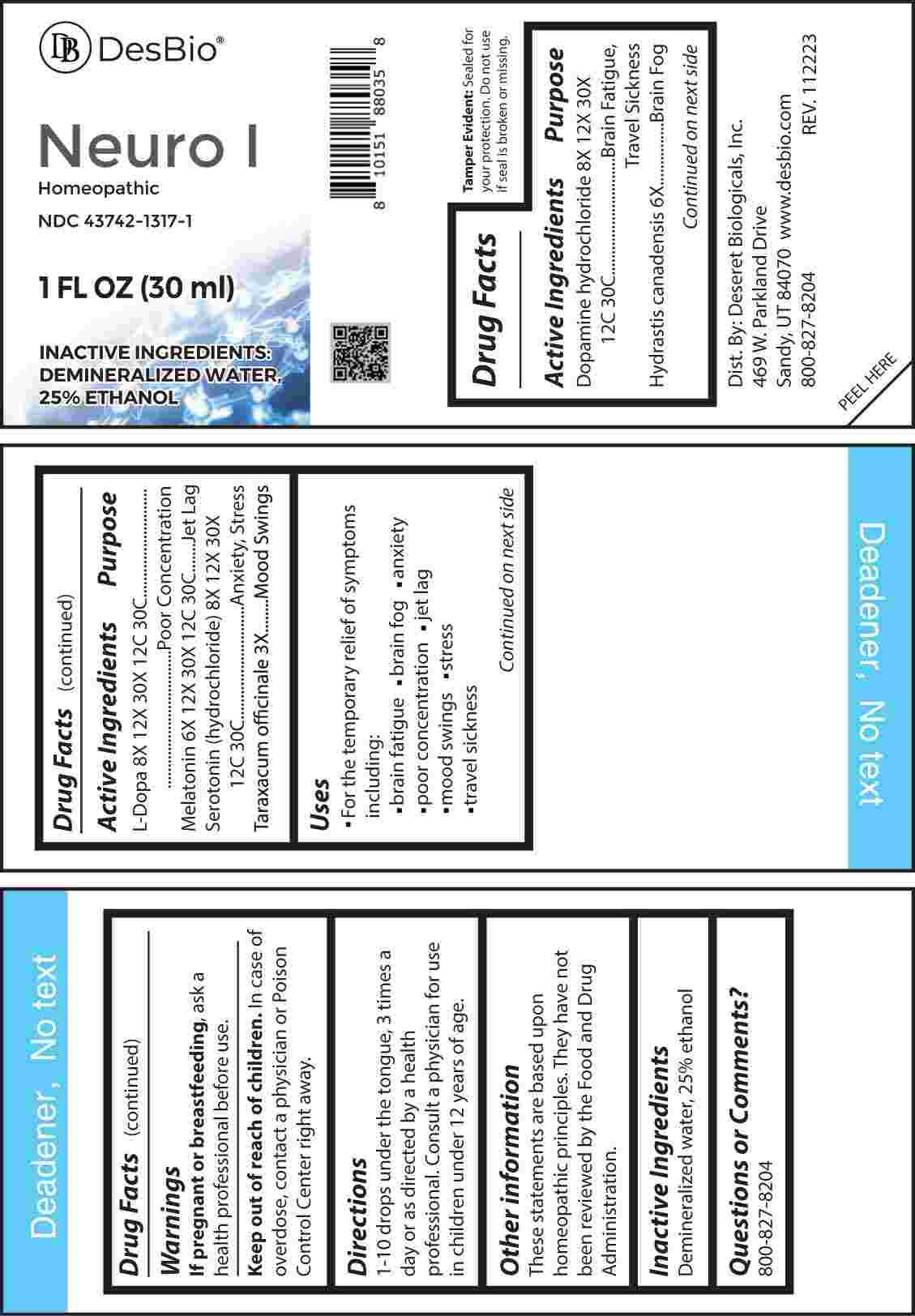 DRUG LABEL: Neuro
NDC: 43742-1317 | Form: LIQUID
Manufacturer: Deseret Biologicals, Inc.
Category: homeopathic | Type: HUMAN OTC DRUG LABEL
Date: 20240227

ACTIVE INGREDIENTS: TARAXACUM OFFICINALE 3 [hp_X]/1 mL; GOLDENSEAL 6 [hp_X]/1 mL; MELATONIN 6 [hp_X]/1 mL; DOPAMINE HYDROCHLORIDE 8 [hp_X]/1 mL; LEVODOPA 8 [hp_X]/1 mL; SEROTONIN HYDROCHLORIDE 8 [hp_X]/1 mL
INACTIVE INGREDIENTS: WATER; ALCOHOL

DRUG FACTS:

ACTIVE INGREDIENTS:

Dopamine Hydrochloride 8X, 12X, 30X, 12C, 30C, Hydrastis Canadensis 6X, L-Dopa 8X, 12X, 30X, 12C, 30C, Melatonin 6X, 12X, 30X, 12C, 30C, Serotonin (Hydrochloride) 8X, 12X, 30X, 12C, 30C, Taraxacum Officinale 3X.

PURPOSE:

Dopamine Hydrochloride – Brain Fatigue, Travel Sickness, Hydrastis Canadensis – Brain Fog, L-Dopa – Poor Concentration, Melatonin – Jet Lag, Serotonin (Hydrochloride) – Anxiety, Stress, Taraxacum Officinale – Mood Swings

USES:

• For the temporary relief of symptoms including:

• brain fatigue • brain fog • anxiety

• poor concentration • jet lag

• mood swings • stress • travel sickness

These statements are based upon homeopathic principles. They have not been reviewed by the Food and Drug Administration.

WARNINGS:

If pregnant or breast-feeding, ask a health professional before use.

Keep out of reach of children. In case of overdose, contact a physician or Poison Control Center right away.

Tamper Evident: Sealed for your protection. Do not use if seal is broken or missing.

KEEP OUT OF REACH OF CHILDREN:

In case of overdose, contact a physician or Poison Control Center right away.

DIRECTIONS:

1-10 drops under the tongue, 3 times a day or as directed by a health professional. Consult a physician for use in children under 12 years of age.

INACTIVE INGREDIENTS:

Demineralized water, 25% ethanol

QUESTIONS:

Dist. By: Deseret Biologicals, Inc.
469 W. Parkland Drive
Sandy, UT 84070

www.desbio.com

800-827-8204

PACKAGE LABEL DISPLAY:

Des Bio

Neuro I

Homeopathic

NDC 43742-1317-1

1 FL OZ (30 ml)